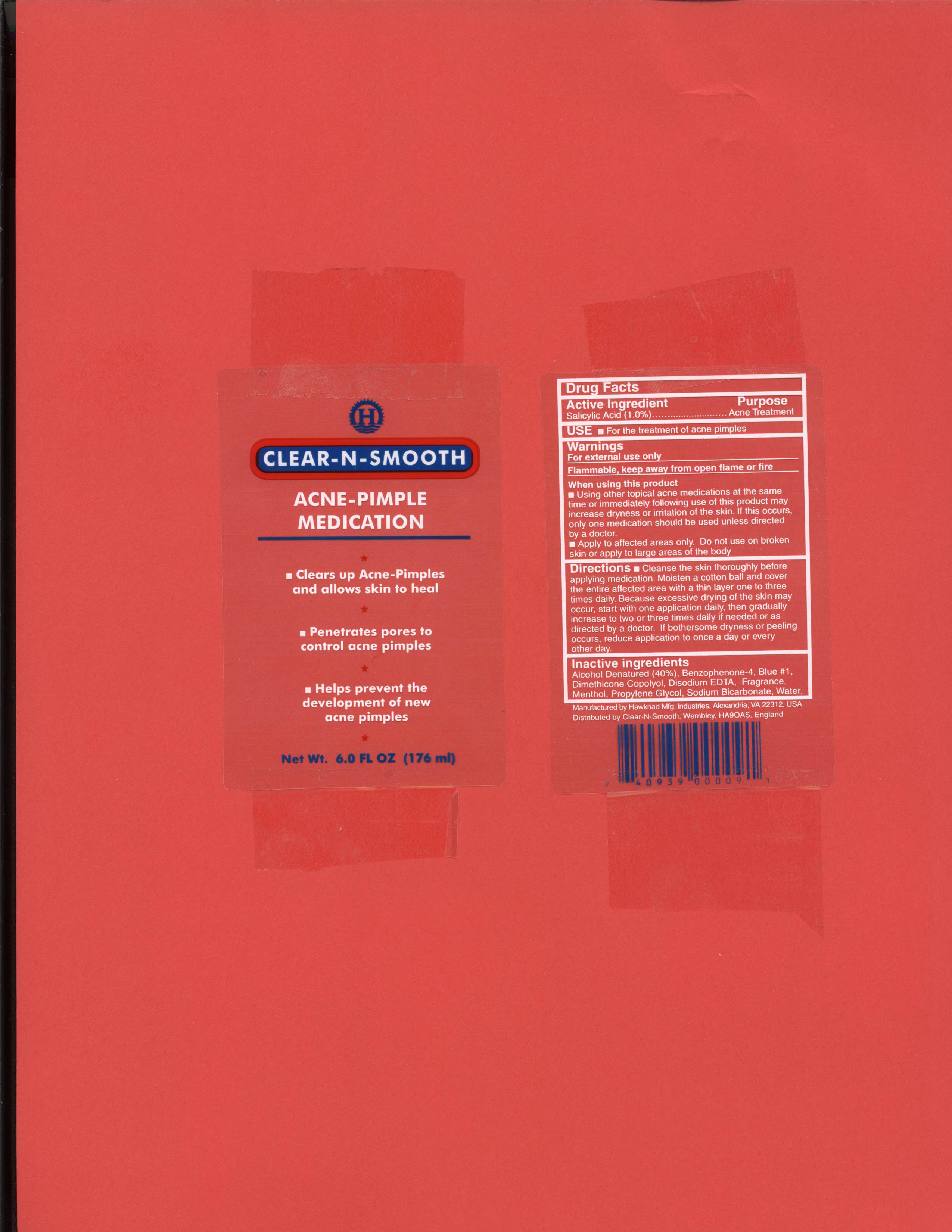 DRUG LABEL: Clear-N-Smooth
NDC: 76445-0091 | Form: LOTION
Manufacturer: Hawknad Manufacturing Industries, Inc.
Category: otc | Type: HUMAN OTC DRUG LABEL
Date: 20230110

ACTIVE INGREDIENTS: SALICYLIC ACID 0.01 g/1 g
INACTIVE INGREDIENTS: ALCOHOL 0.45 g/1 g; WATER 0.49 g/1 g; PROPYLENE GLYCOL 0.02 g/1 g; SODIUM BICARBONATE 0.01 g/1 g; SULISOBENZONE 0.001 g/1 g; FD&C BLUE NO. 1 0.00005 g/1 g; DIMETHICONOL (40 CST) 0.005 g/1 g; EDETATE DISODIUM 0.001 g/1 g; LEVOMENTHOL 0.0005 g/1 g

Listing for Clear-N-Smooth Acne-Pimple Medication

Indications for Use

For the Treatment of Acne Pimples

Purpose

Acne Treatment

Dosage

Moisten a cotton ball and apply a thin layer over the entire affected area.

Keep Out of Reach of Children

For External Use Only. Keep Out of reach of Children.

Warnings

For External Use Only

Flammable. Keep away from open flame or fire.

When Using this Product

- using other topical acne medications at the same time or immediately following use of this product may increase dryness or irritation of the skin. If this occurs, only one acne medication should be used unless directed by a doctor.
- Apply to affected areas only. Do not use on broken skin or apply to large areas of the body.

Instructions for Use

Cleanse the skin thoroughly before applying medication. Moisten a cotton ball with the lotion and cover the entire affected area with a thin layer one to three times daily. Because excessive drying of the skin may occur, start with one application daily then gradually increase to two or three times daily if needed or as directed by a doctor. If bothersome dryness or peeling occurs, reduce application to once a day or every other day.

Inactive Ingredients

alcohol, water, propylene glycol, dimethicone copolyol, disodium EDTA, benzophenone-4, menthol, sodium bicarbonate, blue #1, fragrance.

Active Ingredient

Salicylic Acid - 1.0%